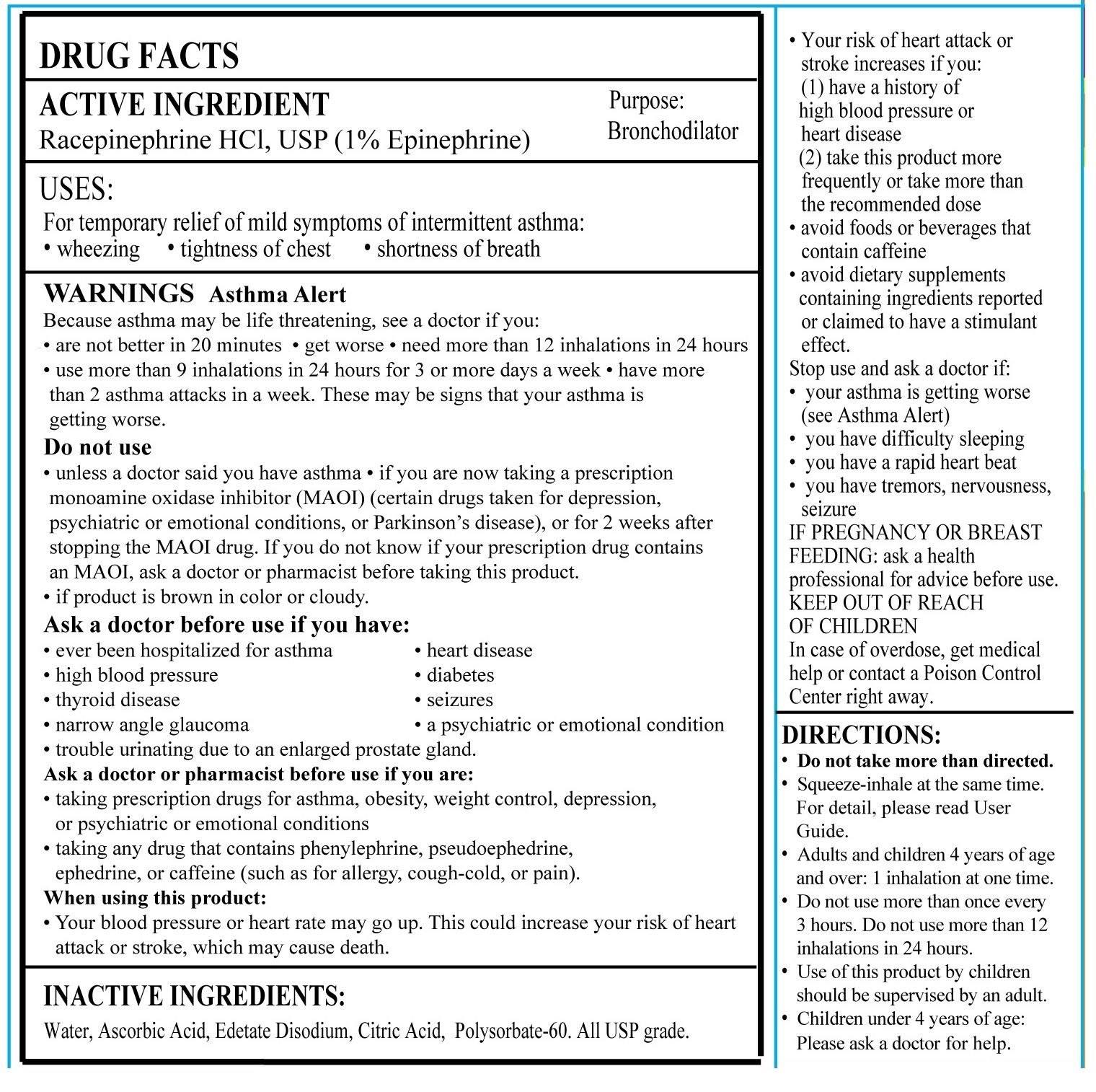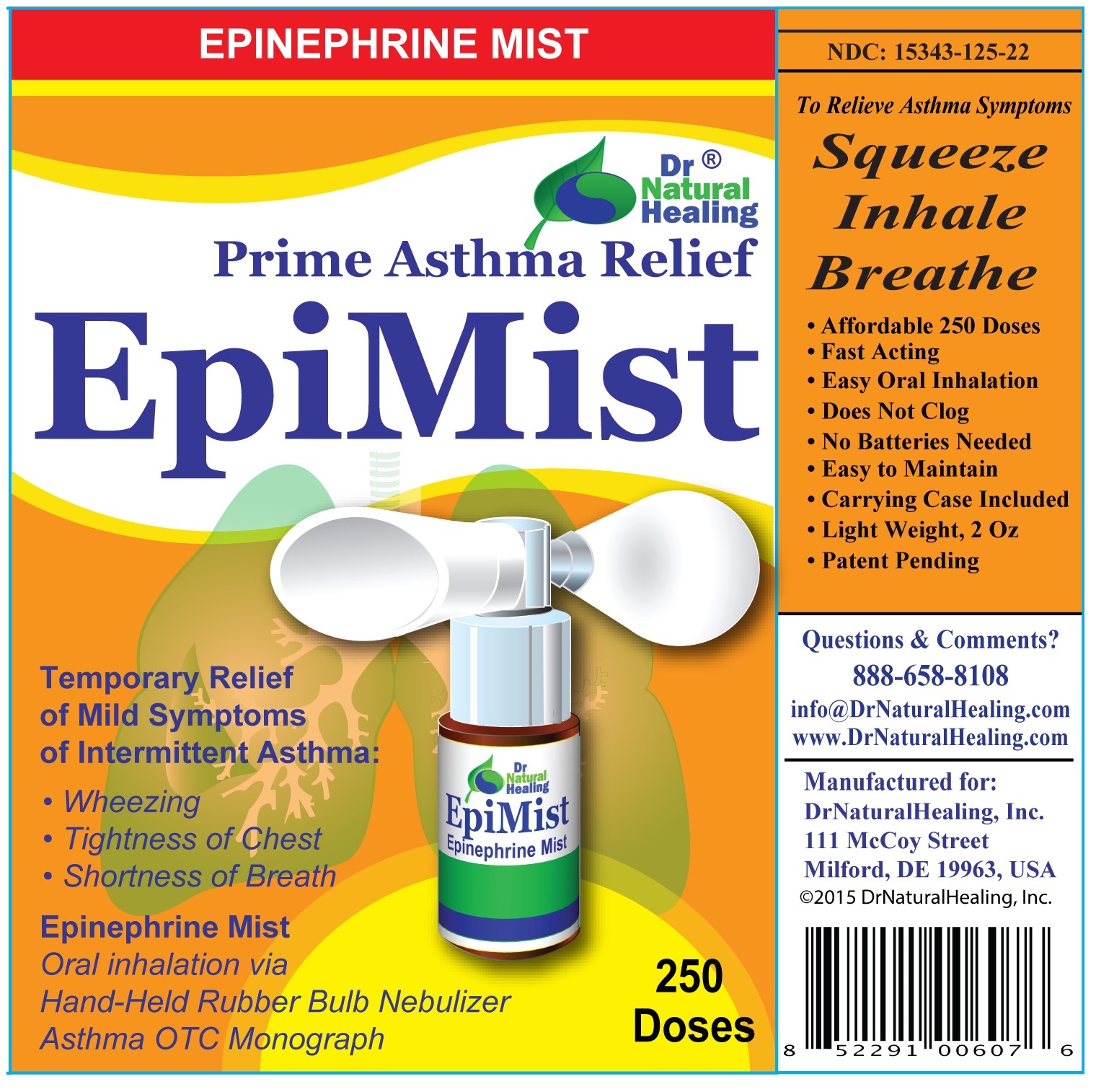 DRUG LABEL: Epi-Mist
NDC: 15343-125 | Form: AEROSOL, SPRAY
Manufacturer: DRNATURALHEALING INC
Category: otc | Type: HUMAN OTC DRUG LABEL
Date: 20180320

ACTIVE INGREDIENTS: RACEPINEPHRINE HYDROCHLORIDE .594 mg/.120 mL
INACTIVE INGREDIENTS: WATER .11808 mL/.120 mL; SODIUM CHLORIDE 1.08 mg/.120 mL; SODIUM CITRATE .120 mg/.120 mL; CITRIC ACID MONOHYDRATE .140 mg/.120 mL

Prime Asthma Relief EpiMist

ACTIVE INGREDIENT

ACTIVE INGREDIENT: Racepinephrine HCL, USP (1% Epinephrine)

PURPOSE

BRONCHODILATOR

DOSAGE AND ADMINISTRATION

DIRECTIONS
• Do not take more than directed
• Place your lips around the mouthpiece and squeeze the bulb while inhaling simultaneously to breathe in the epinephrine aerosol– see figure below for details
• Adults and children 4 years of age and over: Do not take more than one dose every 3 hours. Do not take more than 8 doses in a 24-hour period. The use of this product by children under the age of 12 should be supervised by an adult.
• For children’s usage between 4 to 12 years of age: an adult may squeeze the bulb while your child inhales.
• Please contact your doctor if your symptoms advance.

How Supplied

Each unit of EpiMist contains 10 ml, 250 doses of epinephrine. Each dose (40 microliters) is delivered by one (1) turn-click of the device, containing 1% epinephrine solution made with racepinephrine hydrogen chloride, USP.

Storage and Handling

1) Protect from light to reduce loss of the activity of the active ingredient.
2) Avoid excessive heat.
3) You can carry the whole set during daytime but avoid excessive heat and bright light.
4) When at home, it is recommended to store in refrigerator (35 to 40 oF).
5) After the liquid medicine is used out, dispose the plastic device properly.

Inactive Ingredient Section

INACTIVE INGREDIENT
Water, Edetate Disodium, Ascorbic Acid, Citric Acid, Polysobate-60. All USP grade.

KEEP OUT OF REACH OF CHILDREN

Keep out of reach of children. In case of overdose, get medical help or contact a Poison Control Center right away